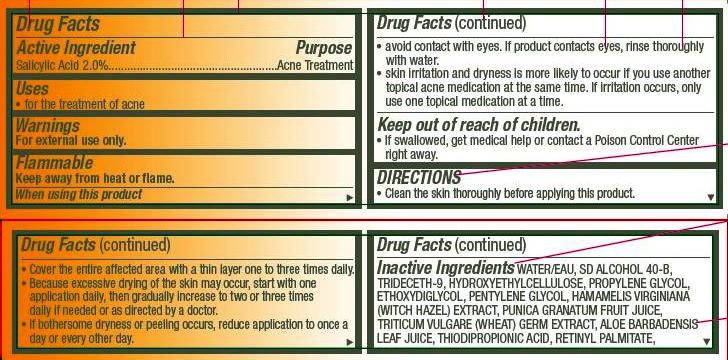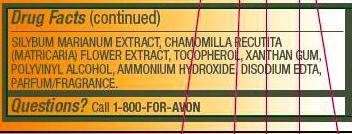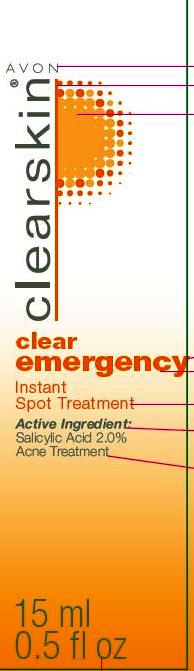 DRUG LABEL: clearskin
NDC: 10096-0276 | Form: GEL
Manufacturer: Avon Products, Inc.
Category: otc | Type: HUMAN OTC DRUG LABEL
Date: 20120420

ACTIVE INGREDIENTS: SALICYLIC ACID 0.3 mL/15 mL

Drug Facts

Active Ingredient
Salicylic Acid 2.0%..................

Purpose
......................Acne Treatment

Uses
• for the treatment of acne

Warnings
For external use only.

STORAGE AND HANDLING

Flammable
Keep away from heat or flame.

When using this product

• avoid contact with eyes. If product contacts eyes, rinse thoroughly with water.
• skin irritation and dryness is more likely to occur if you use another topical acne medication at the same time. If irritation occurs, only use one topical medication at a time.

Keep out of reach of children.
• If swallowed, get medical help or contact a Poison Control Center
right away.

DIRECTIONS
• Clean the skin thoroughly before applying this product.

• Cover the entire affected area with a thin layer one to three times daily.
• Because excessive drying of the skin may occur, start with one application daily, then gradually increase to two or three times daily if needed or as directed by a doctor.
• If bothersome dryness or peeling occurs, reduce application to once a day or every other day.

INACTIVE INGREDIENT

Inactive Ingredients WATER/EAU, SD ALCOHOL 40-B, TRIDECETH-9, HYDROXYETHYLCELLULOSE, PROPYLENE GLYCOL, ETHOXYDIGLYCOL, PENTYLENE GLYCOL, HAMAMELIS VIRGINIANA (WITCH HAZEL) EXTRACT, PUNICA GRANATUM FRUIT JUICE, TRITICUM VULGARE (WHEAT) GERM EXTRACT, ALOE BARBADENSIS LEAF JUICE, THIODIPROPIONIC ACID, RETINYL PALMITATE, SILYBUM MARIANUM EXTRACT, CHAMOMILLA RECUTITA (MATRICARIA) FLOWER EXTRACT, TOCOPHEROL, XANTHAN GUM, POLYVINYL ALCOHOL, AMMONIUM HYDROXIDE, DISODIUM EDTA, PARFUM/FRAGRANCE.

Questions? Call 1-800-FOR-AVON